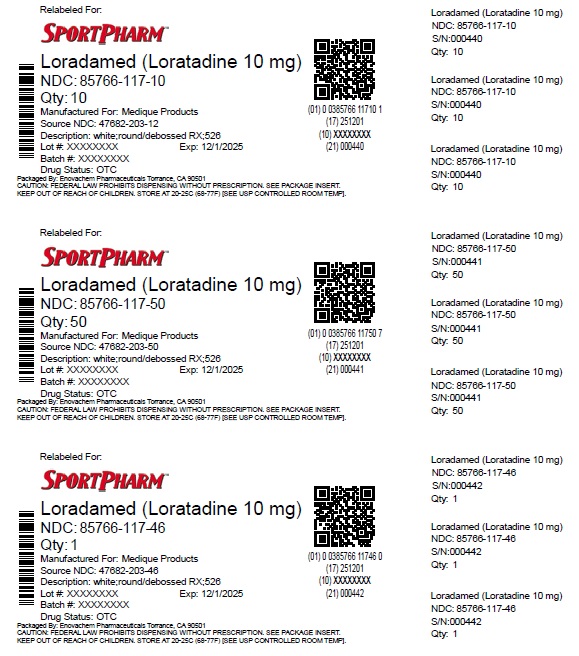 DRUG LABEL: MEDIQUE Loradamed
NDC: 85766-117 | Form: TABLET, FILM COATED
Manufacturer: Sportpharm, Inc. dba Sportpharm
Category: otc | Type: HUMAN OTC DRUG LABEL
Date: 20251202

ACTIVE INGREDIENTS: LORATADINE 10 mg/1 1
INACTIVE INGREDIENTS: LACTOSE MONOHYDRATE; MAGNESIUM STEARATE; STARCH, CORN

Medique Loradamed

Drug Facts

Active ingredient (in each tablet)

Loratadine 10 mg

Purpose

Antihistamine

Uses

Temporarily relieves these symptoms due to hay fever or other upper respiratory allergies

- runny nose
- itchy, watery eyes
- sneezing
- itching of the nose or throat

Warnings

DO NOT USE

Do not useif you have ever had an allergic reaction to this product or any of its ingredients.

Ask a doctor before use if you haveliver or kidney disease.

Your doctor should determine if you need a different dose.

WHEN USING

When using this productdo not take more than directed.

Taking more than directed may cause drowsiness.

Stop use and ask a doctor if

- an allergic reaction to this product occurs. Seek medical help right away.

PREGNANCY OR BREAST FEEDING

If pregnant or breast-feeding, ask a health professional before use.

Keep out of reach of children.In case of overdose, get medical help or contact a Poison Control Center right away (1-800-222-1222).

Directions

Adults and children (6 years and over)

1 tablet daily, not more than 1 tablet in 24 hours.

Children under 6 years:

Ask a doctor

Consumer with liver or kidney disease:

Ask a doctor

Other information

- store between 68º and 77ºF (20º and 25ºC)
- protect from excessive moisture
- tamper evident sealed packets
- do not use any opened or torn packets

Inactive ingredients

corn starch*, lactose monohydrate, magnesium stearate, pregelatinized corn starch*, pregelatinized starch*, sodium starch glycolate*

* may contain

Questions or comments?Call 1-800-634-7680